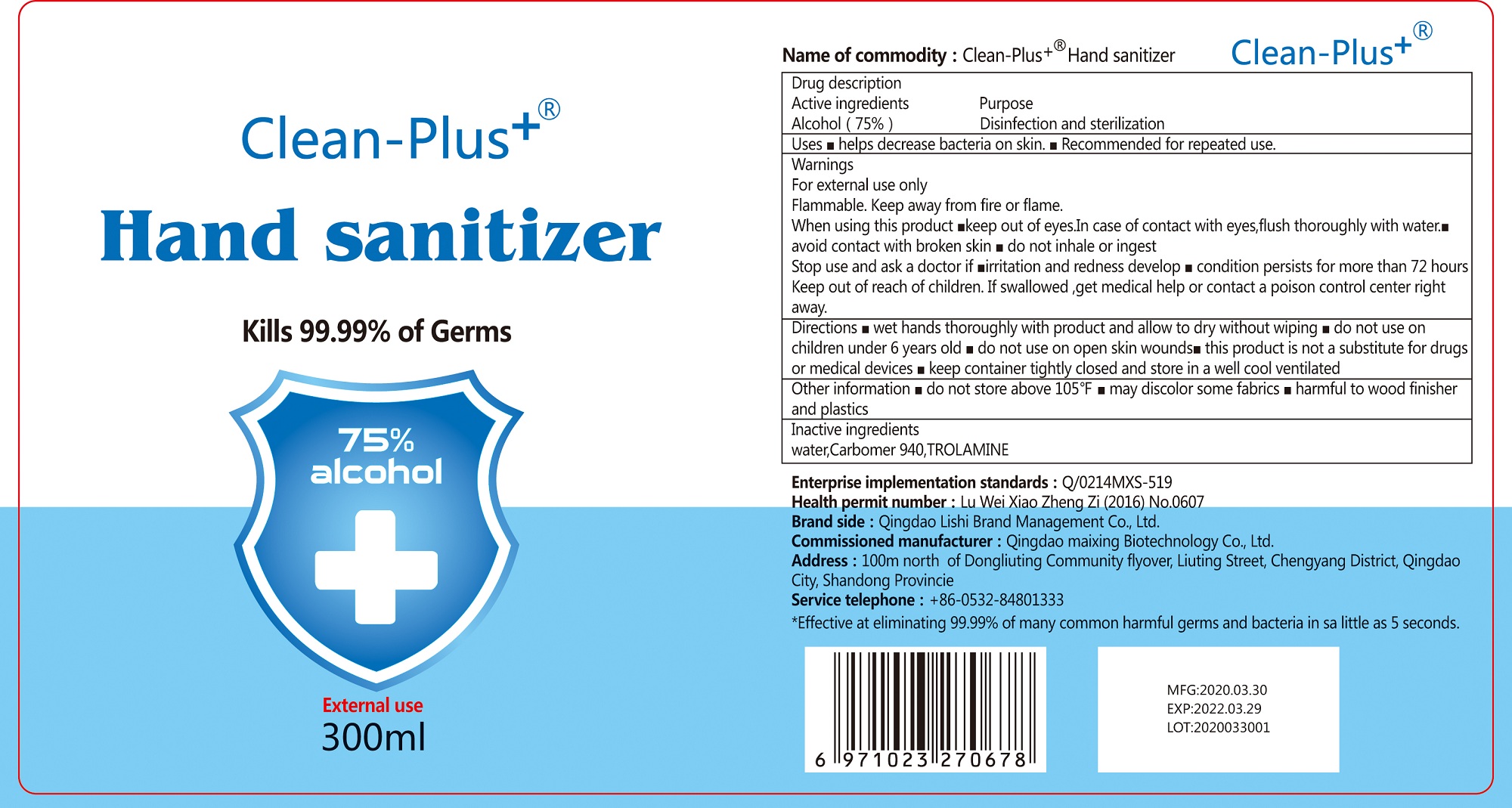 DRUG LABEL: Alcohol Disinfectant
NDC: 75711-002 | Form: GEL
Manufacturer: Qingdao Maixing Biotechnology Co.,Ltd
Category: otc | Type: HUMAN OTC DRUG LABEL
Date: 20200422

ACTIVE INGREDIENTS: ALCOHOL 225 mL/300 mL
INACTIVE INGREDIENTS: WATER; CARBOMER 940 1.05 mL/300 mL; TROLAMINE 0.6 mL/300 mL

Hand Sanitizer

This is a hand sanitizer manufactured according to the Temporary Policy for Preparation of Certain Alcohol-Based Hand Sanitizer Products During the Public Health Emergency (CoViD-19); Guidance for Industry.

The hand sanitizer is manufactured using only the following United States Pharmacopoeia (USP) grade ingredients in the preparation of the product (percentage in final product formulation) consistent with World Health Organization (WHO) recommendations:

1. Alcohol (ethanol) (USP or Food Chemical Codex (FCC) grade) (75%, volume/volume (v/v)) in an aqueous solution denatured according to Alcohol and Tobacco Tax and Trade Bureau regulations in 27 CFR part 20.
2. Sterile distilled water or boiled cold water.

The firm does not add other active or inactive ingredients. Different or additional ingredients may impact the quality and potency of the product.

Active Ingredient(s)

Alcohol 75% v/v. Purpose:disinfection and sterilization

Purpose

Antiseptic, Hand Sanitizer.

disinfection and sterilization

Use

helps decrease bacteria on skin.recommended for repeated use.

Warnings

For external use only. Flammable. Keep away from fire or flame.

- do not use on children under 6 years old.
- do not use on open skin wounds.

WHEN USING

- keep out of eyes.in case of contact with eyes,flush thoroughly with water
- avoid contact with broken skin
- do not inhale or ingest

STOP USE

irritation and redness develop
condition persists for more tahn 72 hours

KEEP OUT OF REACH OF CHILDREN

if swallowed, get medical help or contact a poison control center right away

Directions

wet hands thoroughly with product and allow to dry without wiping.

this product is not a substitute for drugs or medical devices.

keep container tightly closed and store in a well cool ventilated.

Other information

- do not store above 105.F
- may discolor some fabrics
- harmful to wood finisher and plastics

Inactive ingredients

water,carbomer940,trolamine

Package Label - Principal Display Panel

300 mL NDC: